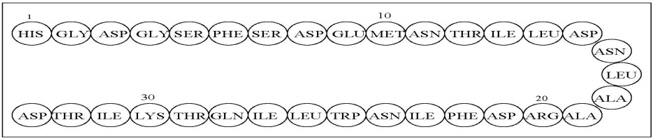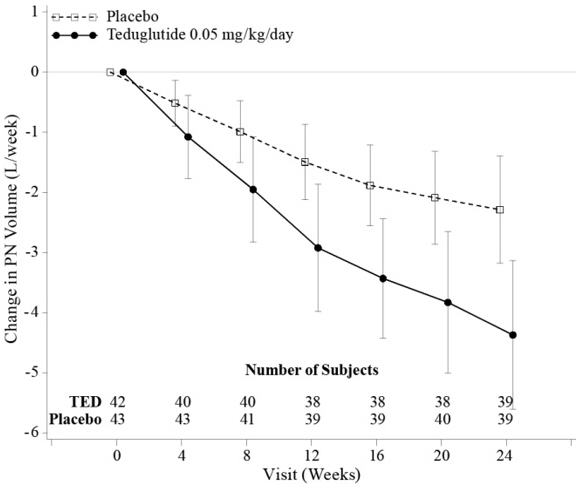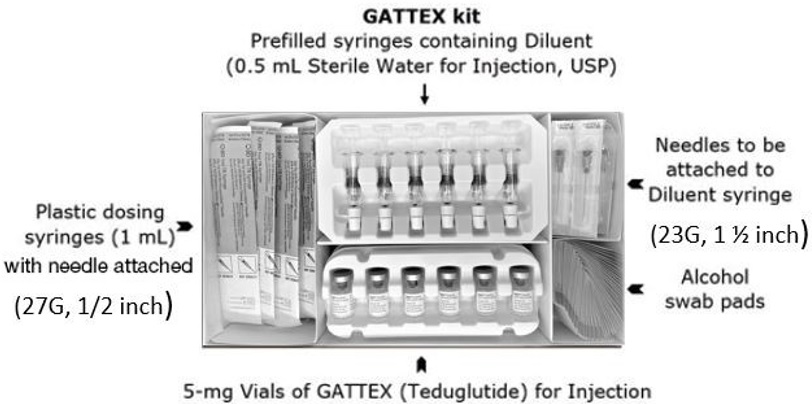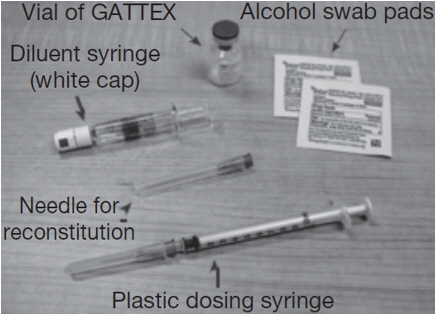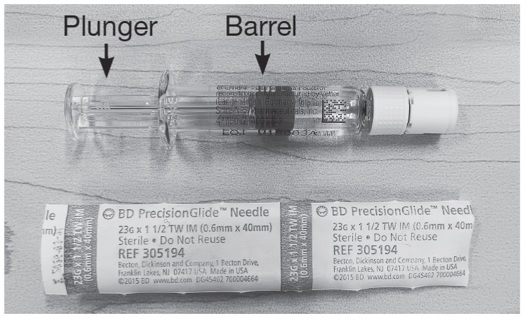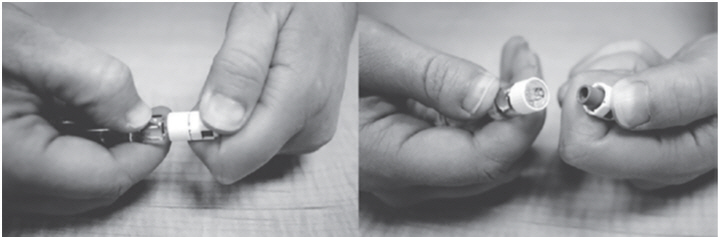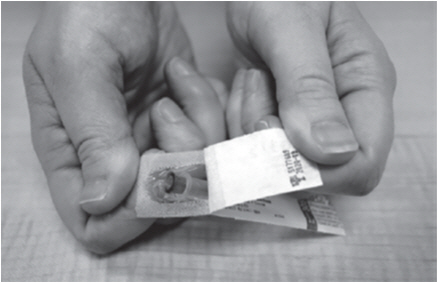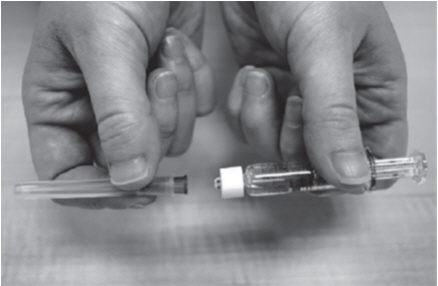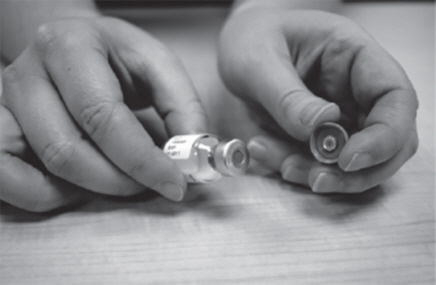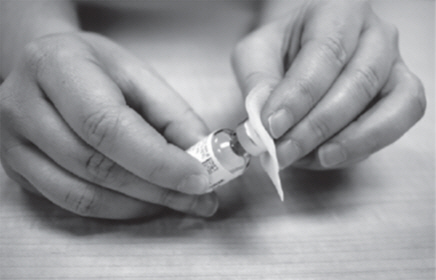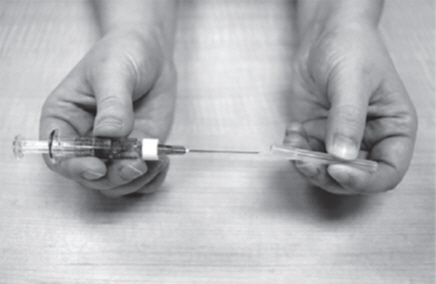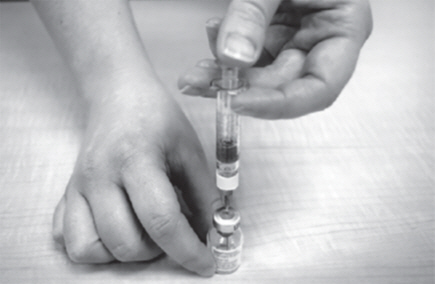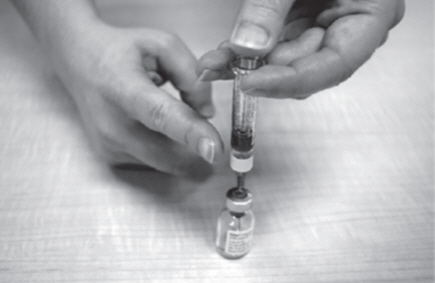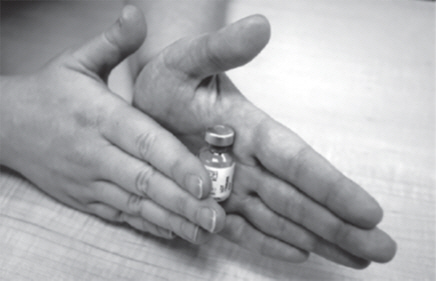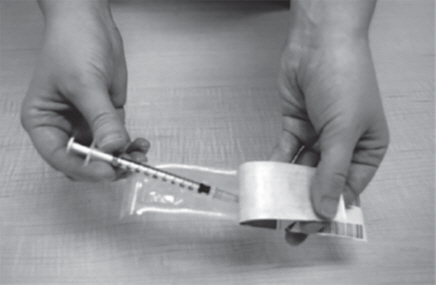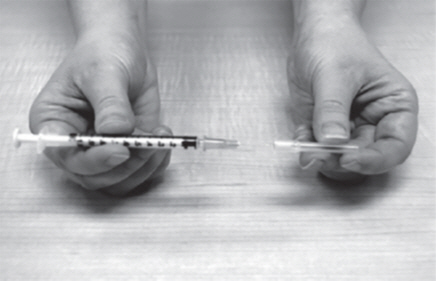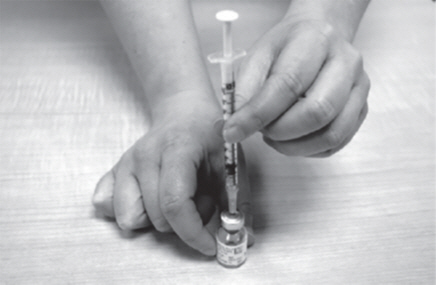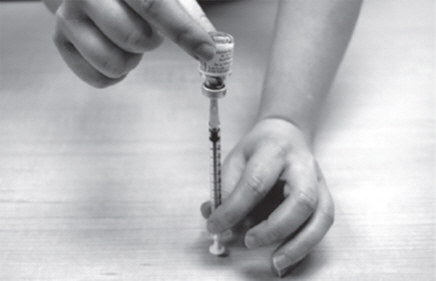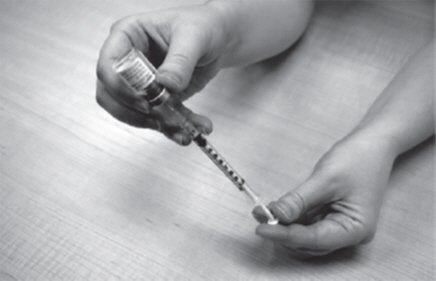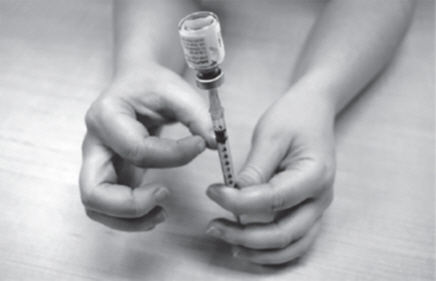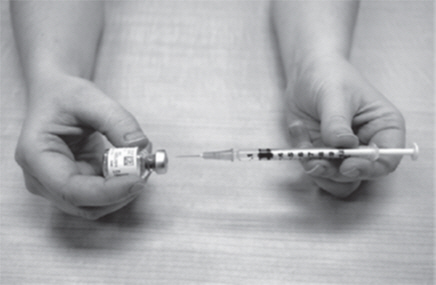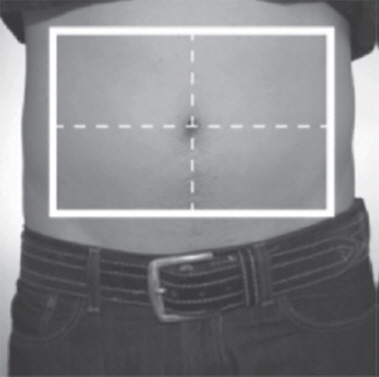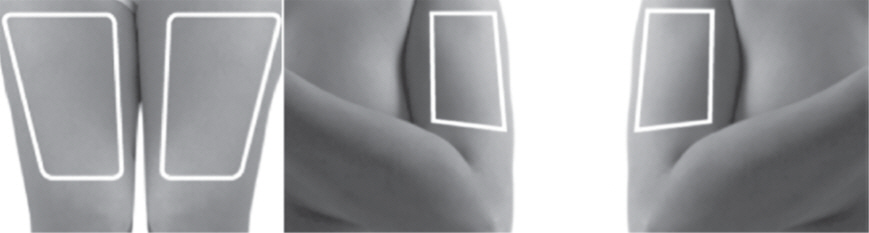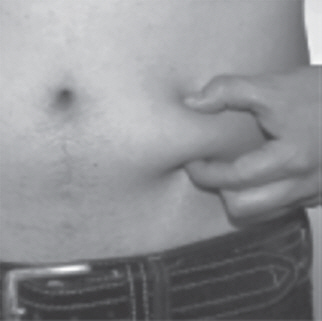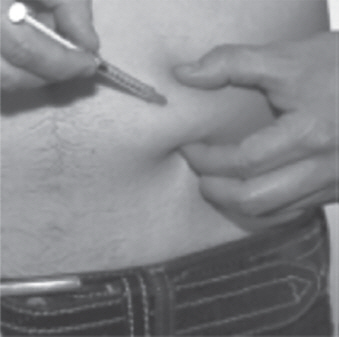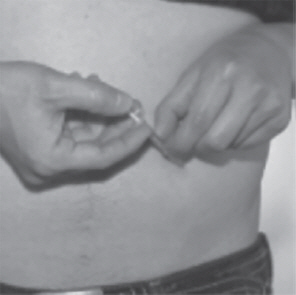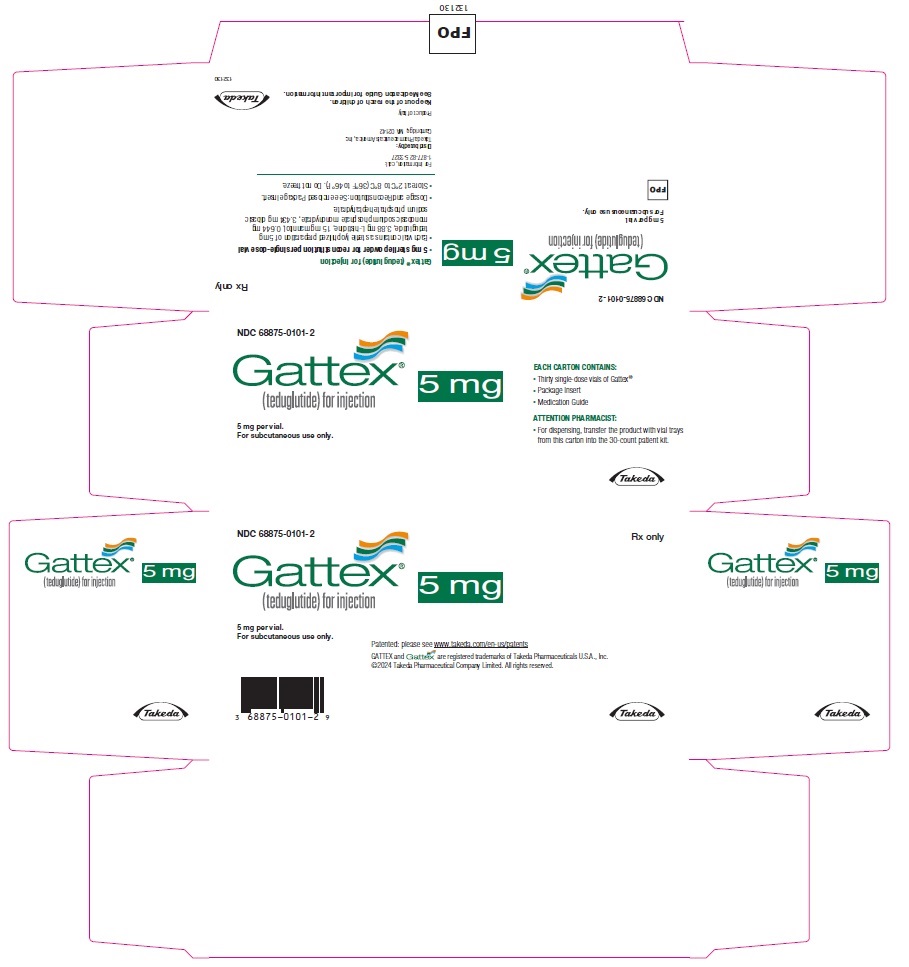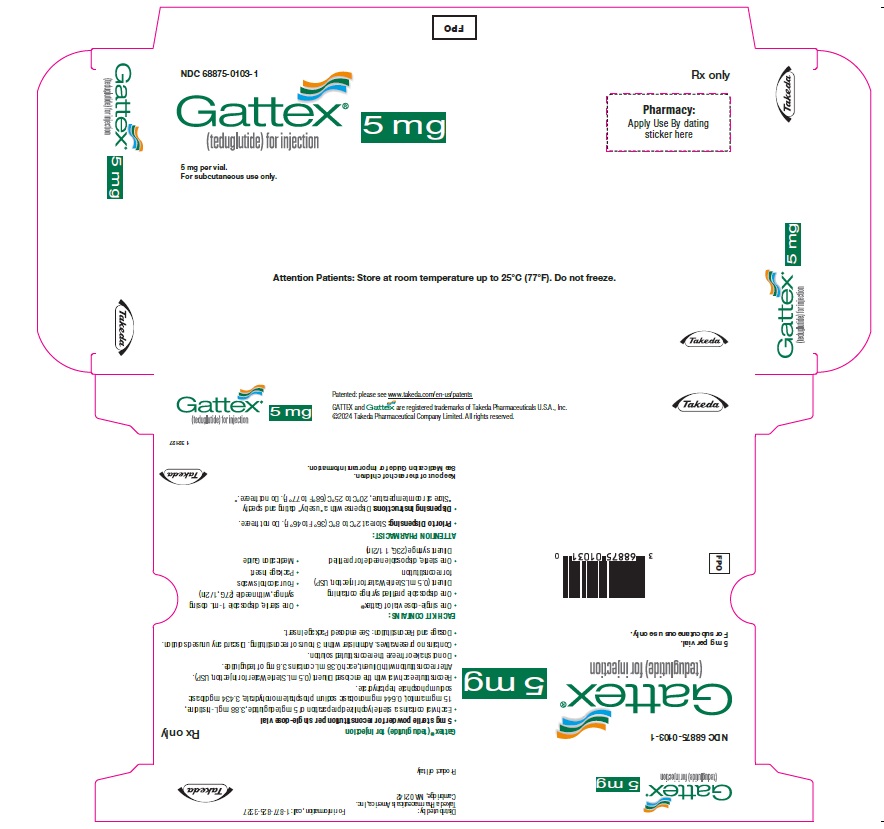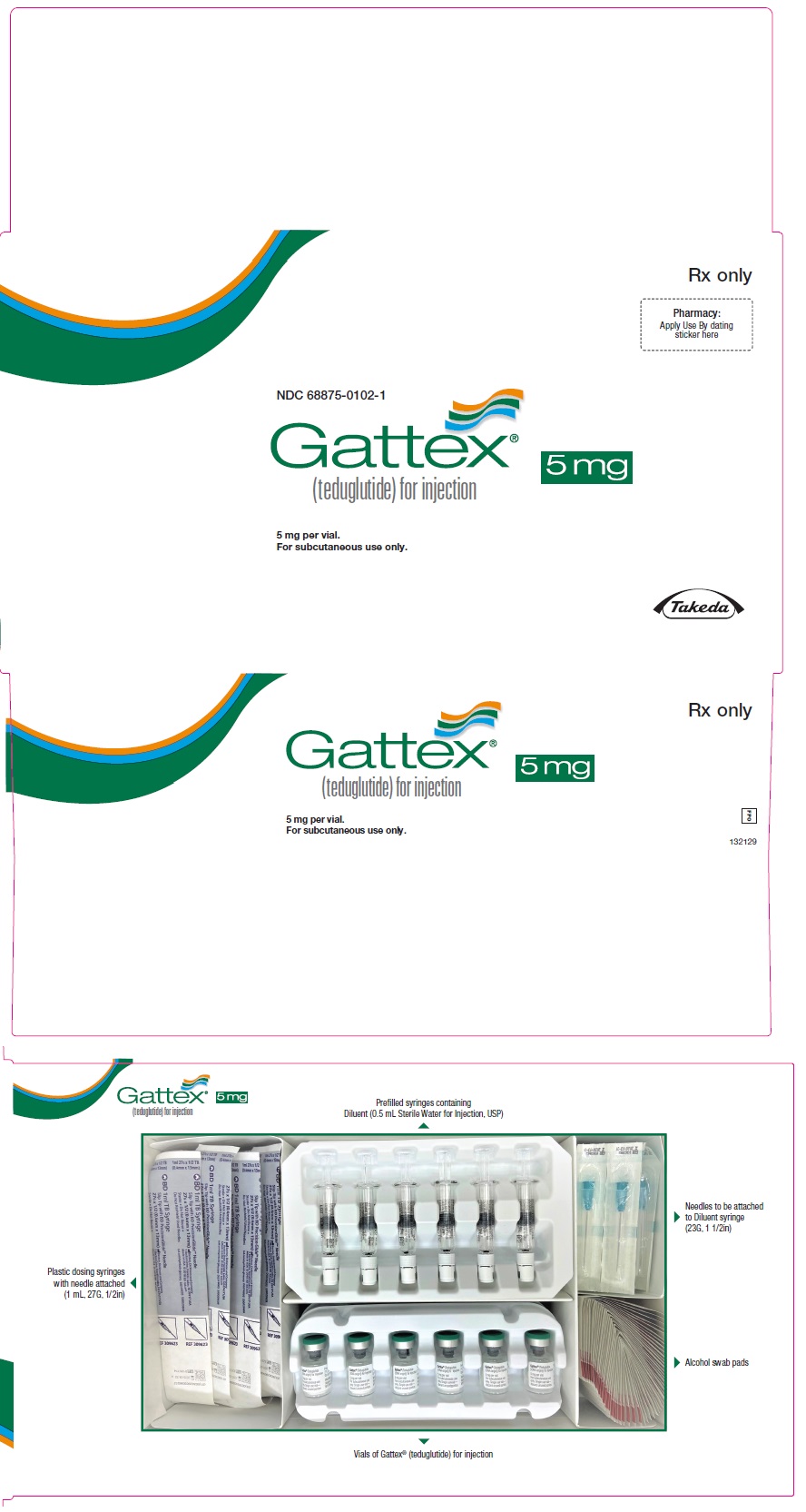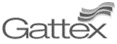 DRUG LABEL: Gattex
NDC: 68875-0101 | Form: INJECTION, POWDER, LYOPHILIZED, FOR SOLUTION
Manufacturer: Takeda Pharmaceuticals America, Inc.
Category: prescription | Type: HUMAN PRESCRIPTION DRUG LABEL
Date: 20250905

ACTIVE INGREDIENTS: teduglutide 5 mg/0.5 mL
INACTIVE INGREDIENTS: Histidine 3.88 mg/0.5 mL; mannitol 15 mg/0.5 mL; sodium phosphate, monobasic, monohydrate 0.644 mg/0.5 mL; sodium phosphate, dibasic, heptahydrate 3.434 mg/0.5 mL

HIGHLIGHTS OF PRESCRIBING INFORMATION

These highlights do not include all the information needed to use GATTEX safely and effectively. See full prescribing information for GATTEX.
GATTEX® (teduglutide) for injection, for subcutaneous use
Initial U.S. Approval: 2012

1 INDICATIONS AND USAGE

GATTEX® is a glucagon-like peptide-2 (GLP-2) analog indicated for the treatment of adults and pediatric patients 1 year of age and older with Short Bowel Syndrome (SBS) who are dependent on parenteral support. (1)

2 DOSAGE AND ADMINISTRATION

Important Administration Information

GATTEX is for adult self-administration or caregiver administration. Self-administration in pediatric patients has not been tested. Use of the GATTEX 5 mg kit is not recommended in pediatric patients weighing less than 10 kg. (2.1)

Evaluation Testing within 6 Months Prior to Starting GATTEX

- Adult Patients: Perform a colonoscopy and upper GI endoscopy with removal of polyps. (2.1, 5.1)
- Pediatric Patients: Perform fecal occult blood testing. If new or unexplained blood in the stool, perform colonoscopy/sigmoidoscopy and upper GI endoscopy. (2.1, 5.1)
- Adult and Pediatric Patients: Obtain baseline laboratory assessments (bilirubin, alkaline phosphatase, lipase and amylase). (2.1, 5.3)

Dosage and Administration

- For subcutaneous use only. (2.2)
- The recommended dosage of GATTEX for both adults and pediatric patients is 0.05 mg/kg once daily by subcutaneous injection. (2.2)
- Alternate sites between 1 of the 4 quadrants of the abdomen, or into alternating thighs or alternating arms. (2.2)

Dosage Adjustment for Renal Impairment

- For adult and pediatric patients with moderate and severe renal impairment and end-stage renal disease (estimated glomerular filtration rate less than 60 mL/min/1.73 m^2) the recommended dosage is 0.025 mg/kg once daily. (2.3)

Discontinuation

- When treatment is discontinued, monitor for fluid and electrolyte imbalances. (2.5, 5.4)

Preparation

- See full prescribing information for instructions on reconstitution. (2.6)

3 DOSAGE FORMS AND STRENGTHS

For injection: 5 mg teduglutide in a single-dose vial supplied with 0.5 mL Sterile Water for Injection in a single-dose prefilled syringe. (3)

4 CONTRAINDICATIONS

None. (4)

5 WARNINGS AND PRECAUTIONS

- Acceleration of Neoplastic Growth: In case of intestinal malignancy, discontinue GATTEX. The decision to continue GATTEX in patients with non-gastrointestinal malignancy should be made based on benefit risk considerations. (5.1)
  - In adult patients, colonoscopy and upper GI endoscopy (or alternate imaging) is recommended after 1 year of treatment. Perform subsequent colonoscopies and upper GI endoscopes (or alternate imaging) no less frequently than every 5 years. (5.1)
  - In pediatric patients, perform fecal occult blood testing annually. Colonoscopy/sigmoidoscopy is recommended after 1 year of treatment and every 5 years thereafter on treatment. Consider upper GI endoscopy (or alternate imaging) during treatment with GATTEX. (5.1)
- Intestinal Obstruction: In patients who develop intestinal or stomal obstruction, temporarily discontinue GATTEX pending further clinical evaluation and management. (5.2)
- Biliary and Pancreatic Disease: Obtain bilirubin, alkaline phosphatase, lipase, amylase every 6 months. If clinically meaningful changes are seen, further evaluation is recommended including imaging, and reassess continued GATTEX treatment. (5.3)
- Fluid Overload, Including Congestive Heart Failure: If fluid overload occurs, adjust parenteral support, and reassess continued GATTEX treatment. (5.4)
- Potential for Increased Absorption of Oral Medications: Monitor patients on concomitant oral medications (e.g., benzodiazepines) for adverse reactions related to the concomitant drug; dosage reduction of the other drug may be required. (5.5, 7.1)

6 ADVERSE REACTIONS

Most common adverse reactions (≥10%) are: abdominal pain, nausea, upper respiratory tract infection, abdominal distension, injection site reaction, vomiting, fluid overload, and hypersensitivity. (6.1)

To report SUSPECTED ADVERSE REACTIONS, contact Takeda Pharmaceuticals U.S.A., Inc. at 1-877-TAKEDA-7 (1-877-825-3327) or FDA at 1-800-FDA-1088 or www.fda.gov/medwatch.

8 USE IN SPECIFIC POPULATIONS

Lactation: Breastfeeding not recommended. (8.2)

FULL PRESCRIBING INFORMATION

1 INDICATIONS AND USAGE

GATTEX® is indicated for the treatment of adults and pediatric patients 1 year of age and older with Short Bowel Syndrome (SBS) who are dependent on parenteral support.

2 DOSAGE AND ADMINISTRATION

2.1 Important Administration Information

GATTEX is for adult self-administration or caregiver administration. Self-administration in pediatric patients has not been tested.

Use of the GATTEX 5 mg kit is not recommended in pediatric patients weighing less than 10 kg.

Evaluation and testing prior to starting treatment with GATTEX:

Within 6 months prior to treatment:

Adult patients

- Perform a colonoscopy and an upper gastrointestinal (GI) endoscopy with removal of polyps [see Warnings and Precautions (5.1)].
- Obtain baseline laboratory assessments (bilirubin, alkaline phosphatase, lipase and amylase) [see Warnings and Precautions (5.3)].

Pediatric patients

- Perform fecal occult blood testing; if there is new or unexplained blood in the stool, perform colonoscopy/sigmoidoscopy and an upper GI endoscopy [see Warnings and Precautions (5.1)].
- Obtain baseline laboratory assessments (bilirubin, alkaline phosphatase, lipase and amylase) [see Warnings and Precautions (5.3)].

2.2 Recommended Dosage and Administration for Adults and Pediatric Patients 1 Year of Age and Older

GATTEX is for subcutaneous injection only. Not for intravenous or intramuscular administration.

The recommended dosage of GATTEX is 0.05 mg/kg once daily administered by subcutaneous injection.

If a dose is missed, that dose should be taken as soon as possible on that day. Do not take 2 doses on the same day.

Alternation of sites for subcutaneous injection is recommended, and can include the thighs, upper arms, and the abdomen.

2.3 Dosage Adjustment for Renal Impairment

The recommended dosage in adult and pediatric patients with moderate and severe renal impairment and end-stage renal disease (estimated glomerular filtration rate (eGFR) less than 60 mL/min/1.73 m^2) is 0.025 mg/kg once daily [see Use in Specific Populations (8.6)].

2.4 Monitoring to Assess Safety

Colonoscopy and Upper GI Endoscopy in Adults

- A follow-up colonoscopy and upper GI endoscopy (or alternate imaging) is recommended at the end of 1 year of GATTEX. If no polyp is found, subsequent colonoscopies and upper GI endoscopies (or alternate imaging) should be done no less frequently than every 5 years. If a polyp is found, adherence to current polyp follow-up guidelines is recommended [see Warnings and Precautions (5.1)].

Colonoscopy and Upper GI Endoscopy in Pediatric Patients

- Perform subsequent fecal occult blood testing annually in pediatric patients while they are receiving GATTEX. If there is new or unexplained blood in the stool, perform colonoscopy/sigmoidoscopy and an upper GI endoscopy [see Warnings and Precautions (5.1)].
- Colonoscopy/sigmoidoscopy is recommended for all pediatric patients after 1 year of treatment and every 5 years thereafter while on continuous treatment with GATTEX.
- Consider upper GI endoscopy (or alternate other imaging) during treatment with GATTEX [see Warnings and Precautions (5.1)].

Laboratory Testing

Laboratory assessments are recommended every 6 months. If any clinically meaningful elevation is seen, further diagnostic workup is recommended as clinically indicated (i.e., imaging of the biliary tract, liver, or pancreas) [see Warnings and Precautions (5.1), (5.3)].

2.5 Discontinuation of Treatment

Discontinuation of treatment with GATTEX may result in fluid and electrolyte imbalance. Monitor fluid and electrolyte status in patients who discontinue GATTEX treatment [see Warnings and Precautions (5.4)].

2.6 Preparation Instructions

- Reconstitute each vial of GATTEX by slowly injecting the 0.5 mL of preservative-free Sterile Water for Injection provided in the prefilled syringe. A 10 mg/mL sterile solution is obtained after reconstitution.
- Allow the vial containing GATTEX and water to stand for approximately 30 seconds and then gently roll the vial between the palms for about 15 seconds. Do not shake the vial.
- Allow the mixed contents to stand for about 2 minutes. Inspect the vial for any undissolved powder. If undissolved powder is observed, gently roll the vial again until all material is dissolved. Do not shake the vial.
- Reconstituted GATTEX is a sterile, clear, colorless to light straw-colored solution, which should be free from particulates. If there is any discoloration or particulates, discard the solution.
- A maximum of 0.38 mL of the reconstituted solution, containing 3.8 mg of teduglutide, can be withdrawn from the vial for dosing.
- If the product remains undissolved after the second attempt, do not use.

Storage of the reconstituted solution

- Administer within 3 hours after reconstitution. Discard any unused portion.
- Do not shake or freeze the reconstituted solution.
- For single use only.

3 DOSAGE FORMS AND STRENGTHS

For Injection: 5 mg teduglutide as a white lyophilized powder for reconstitution in a single-dose vial supplied with 0.5 mL Sterile Water for Injection in a single-dose prefilled syringe.

4 CONTRAINDICATIONS

None.

5 WARNINGS AND PRECAUTIONS

5.1 Acceleration of Neoplastic Growth

Based on the pharmacologic activity and tumor findings in the rat and mouse carcinogenicity studies, GATTEX has the potential to cause hyperplastic changes including neoplasia [see Clinical Pharmacology (12.1), Nonclinical Toxicology (13.1)]. In patients at increased risk for malignancy, the clinical decision to use GATTEX should be considered only if the benefits outweigh the risks. In patients who develop active gastrointestinal malignancy (GI tract, hepatobiliary, pancreatic) while on GATTEX, discontinue GATTEX treatment. In patients who develop active non-gastrointestinal malignancy while on GATTEX, the clinical decision to continue GATTEX should be made based on benefit-risk considerations.

Gastrointestinal Polyps

Intestinal polyps were identified during the clinical studies. Postmarketing cases of colorectal, gastric, and small intestinal (duodenum, ileum, and jejunum) polyps have been reported postmarketing [see Adverse Reactions (6.1, 6.2)].

Adult Patients

- Within 6 months prior to starting treatment with GATTEX, perform colonoscopy and upper GI endoscopy with removal of polyps.
- A follow-up colonoscopy and upper GI endoscopy (or alternate imaging) is recommended at the end of 1 year of GATTEX. Perform subsequent colonoscopies and upper GI endoscopies (or alternate imaging) every 5 years or more often as needed. If a polyp is found, adherence to current polyp follow-up guidelines is recommended.
- If gastrointestinal cancer is diagnosed, discontinue GATTEX therapy.

Pediatric Patients

- Within 6 months prior to starting treatment with GATTEX, perform fecal occult blood testing; if there is new or unexplained blood in the stool, perform colonoscopy/sigmoidoscopy and an upper GI endoscopy.
- Perform subsequent fecal occult blood testing annually in pediatric patients while they are receiving GATTEX. If there is new or unexplained blood in the stool, perform colonoscopy/sigmoidoscopy and an upper GI endoscopy.
- Colonoscopy/sigmoidoscopy is recommended for all pediatric patients after 1 year of treatment and every 5 years thereafter while on continuous treatment with GATTEX [see Dosage and Administration (2.1)].
- Consider upper GI endoscopy (or alternate other imaging) during treatment with GATTEX.
- If gastrointestinal cancer is diagnosed, discontinue GATTEX therapy.

5.2 Intestinal Obstruction

Intestinal obstruction has been reported in clinical studies [see Adverse Reactions (6.1)] and postmarketing. In patients who develop intestinal or stomal obstruction, temporarily discontinue GATTEX while the patient is clinically managed. GATTEX may be restarted when the obstructive presentation resolves, if clinically indicated.

5.3 Biliary and Pancreatic Disease

Gallbladder and Biliary Tract Disease

Cholecystitis, cholangitis, and cholelithiasis have been reported in clinical studies [see Adverse Reactions (6.1)] and postmarketing. For identification of the onset or worsening of gallbladder/biliary disease, obtain laboratory assessment of bilirubin and alkaline phosphatase within 6 months prior to starting GATTEX, and at least every 6 months while on GATTEX; or more frequently if needed. If clinically meaningful changes are seen, further evaluation including imaging of the gallbladder and/or biliary tract is recommended; and reassess the need for continued GATTEX treatment.

Pancreatic Disease

Pancreatitis has been reported in clinical studies [see Adverse Reactions (6.1)]. For identification of onset or worsening of pancreatic disease, obtain laboratory assessments of lipase and amylase within 6 months prior to starting GATTEX, and at least every 6 months while on GATTEX; or more frequently if needed. If clinically meaningful changes are seen, further evaluation such as imaging of the pancreas is recommended; and reassess the need for continued GATTEX treatment.

5.4 Fluid Imbalance and Fluid Overload

Fluid Overload

Fluid overload and congestive heart failure have been observed in clinical studies, which were deemed to be related to enhanced fluid absorption associated with GATTEX [see Adverse Reactions (6.1)]. If fluid overload occurs, adjust parenteral support and reassess GATTEX treatment, especially in patients with underlying cardiovascular disease. If significant cardiac deterioration develops while on GATTEX, reassess the need for continued GATTEX treatment.

Fluid and Electrolyte Imbalance

Discontinuation of treatment with GATTEX may also result in fluid and electrolyte imbalance. Monitor fluid and electrolyte status in patients who discontinue treatment with GATTEX [see Dosage and Administration (2.5)].

5.5 Increased Absorption of Concomitant Oral Medication

In the adult placebo-controlled studies, an analysis of episodes of cognition and attention disturbances was performed for patients on benzodiazepines. One patient receiving prazepam concomitantly with GATTEX 0.05 mg/kg once daily experienced a dramatic deterioration in mental status progressing to coma during the first week of GATTEX therapy. The patient was admitted to the ICU and the prazepam blood concentration was >300 mcg/L. GATTEX and prazepam were discontinued, and coma resolved 5 days later.

Monitor patients receiving concomitant oral drugs requiring titration or with a narrow therapeutic index, for adverse reactions due to potential increased absorption of the concomitant drug. The concomitant drug may require a reduction in dosage [see Drug Interactions (7.1)].

6 ADVERSE REACTIONS

The following serious adverse reactions are described elsewhere in the labeling:

- Acceleration of Neoplastic Growth [see Warnings and Precautions (5.1)]
- Intestinal Obstruction [see Warnings and Precautions (5.2)]
- Biliary and Pancreatic Disease [see Warnings and Precautions (5.3)]
- Fluid Imbalance and Fluid Overload [see Warnings and Precautions (5.4)]

6.1 Clinical Trials Experience

Adults

Because clinical trials are conducted under widely varying conditions, the adverse reaction rates observed cannot be directly compared to rates in other clinical trials and may not reflect the rates observed in clinical practice.

The rates of adverse reactions in 136 adult patients with SBS participating in two randomized, placebo-controlled, 24-week, double-blind clinical studies (Study 1 and Study 3) are summarized in Table 1. Only those reactions with a rate of at least 5% in the GATTEX group, and greater than placebo group, are summarized in Table 1.

Table 1: Common Adverse Reactions [Reported at a rate of at least 5% in the GATTEX group, and greater than the placebo group.] in Adult Patients with SBS in Placebo-Controlled Studies: Studies 1 and 3
Adverse Reaction | Placebo (N=59) (%) | GATTEX 0.05 mg/kg Once Daily (N=77) (%)
Abdominal pain [Includes: Abdominal pain, upper abdominal pain, lower abdominal pain] | 22 | 30
Nausea | 20 | 23
Upper respiratory tract infection [Includes: Upper respiratory tract infection, nasopharyngitis, pharyngitis, sinusitis, laryngitis, rhinitis, viral upper respiratory tract infection] | 12 | 21
Abdominal distension | 2 | 20
Injection site reaction [Includes: Injection site hematoma, injection site erythema, injection site pain, injection site swelling, injection site hemorrhage, injection site discoloration, injection site reaction, injection site rash] | 12 | 13
Vomiting | 10 | 12
Fluid Overload [Includes: Fluid overload, peripheral edema, edema, generalized edema, fluid retention and jugular vein distension] | 7 | 12
Hypersensitivity [Includes: Erythema, rash, dermatitis allergic, pruritus, rash macular, drug eruption, eyelid edema, flushing] | 7 | 10
Flatulence | 7 | 9
Decreased appetite | 3 | 7
Influenza [Includes: Influenza, influenza-like illness] | 2 | 7
Skin hemorrhage [Includes: Hematoma, abdominal wall hematoma, post procedural hematoma, umbilical hematoma, blood blister] | 2 | 5
Cough | 0 | 5
Sleep disturbances [Includes: Insomnia (3 patients) and hypersomnia (1 patient)] | 0 | 5

Adverse Reactions in the Subset of Patients with a Stoma

Among the 53 patients with a stoma in the placebo-controlled studies (Study 1 and Study 3), the percentage of patients with gastrointestinal stoma complication was 42% (13/31) for patients receiving GATTEX 0.05 mg/kg/day and 14% (3/22) for patients receiving placebo.

Pediatric Patients 1 Year to Less Than 17 Years of Age

In two clinical studies of 24-week and 12-week duration, 41 pediatric patients aged 1 year to less than 17 years were treated with GATTEX 0.05 mg/kg/day [see Use in Specific Populations (8.4), Clinical Studies (14.2)]. Overall, the safety profile of GATTEX was similar to that in adults. In the long-term extension studies with mean exposure of 41 weeks, no new safety signals were identified.

Less Common Adverse Reactions

Adverse Reactions of Special Interest

Malignancy

Three patients were diagnosed with malignancy in the SBS clinical studies in adults, all of whom were male and had received GATTEX 0.05 mg/kg/day in Study 2. One patient had a history of abdominal radiation for Hodgkin's disease two decades prior to receiving GATTEX and prior liver lesion on CT scan, and was diagnosed with metastatic adenocarcinoma of unconfirmed origin after 11 months of exposure to GATTEX. Two patients had extensive smoking histories and were diagnosed with lung cancers (squamous and non-small cell) after 12 months and 3 months of GATTEX exposure, respectively [see Warnings and Precautions (5.1)].

Intestinal Polyps

In the adult clinical studies, 14 patients with SBS were diagnosed with polyps of the GI tract after initiation of study treatment. In the SBS placebo-controlled studies, 1/59 (2%) of patients on placebo and 1/109 (1%) of patients on GATTEX 0.05 mg/kg/day were diagnosed with intestinal polyps (inflammatory stomal and hyperplastic sigmoidal after 3 and 5 months, respectively). The remaining 12 polyp cases occurred in the extension studies – 2 colorectal villous adenomas (onset at 6 and 7 months in GATTEX 0.1 mg/kg/day (twice the recommended dose) and 0.05 mg/kg/day dose groups, respectively), 2 hyperplastic polyps (onset 6 months in GATTEX 0.1 mg/kg/day dose group and 24 months in GATTEX 0.05 mg/kg/day dose group), 4 colorectal tubular adenomas (onset between 24 and 29 months in GATTEX 0.05 mg/kg/day dose group), 1 serrated adenoma (onset at 24 months in GATTEX 0.05 mg/kg/day dose group), 1 colorectal polyp biopsy not done (onset at 24 months in GATTEX 0.05 mg/kg/day dose group), 1 rectal inflammatory polyp (onset at 10 months in the GATTEX 0.05 mg/kg/day dose group, and 1 small duodenal polyp (onset at 3 months in GATTEX 0.05 mg/kg/day dose group) [see Warnings and Precautions (5.1)].

In the pediatric clinical studies (up to 69 weeks of exposure), there was one case of cecal polyp that was not biopsied and was not seen on repeat colonoscopy.

Gastrointestinal Obstruction

Overall, in the adult clinical studies, 12 patients with SBS experienced one or more episodes of intestinal obstruction/stenosis: 6 in SBS placebo-controlled studies and 6 in the extension studies. The 6 patients in the placebo-controlled studies were all on GATTEX: 3/77 (4%) on GATTEX 0.05 mg/kg/day and 3/32 (9%) on GATTEX 0.1 mg/kg/day (twice the recommended dose). No cases of intestinal obstruction occurred in the placebo group. Onset ranged from 1 day to 6 months. In the adult extension studies, 6 additional patients (all on GATTEX 0.05 mg/kg/day) were diagnosed with intestinal obstruction/stenosis with onsets ranging from 6 days to 19 months. Two of the 6 patients from the placebo-controlled studies experienced recurrence of obstruction in the extension studies. Of all 8 patients with an episode of intestinal obstruction/stenosis in these extension studies, 2 patients required endoscopic dilation and 1 required surgical intervention) [see Warnings and Precautions (5.2)].

In the pediatric clinical studies (up to 69 weeks of exposure), there was 1 serious adverse reaction of obstruction. Teduglutide was temporarily withheld, obstruction resolved without additional intervention, and there was no recurrence once teduglutide was restarted.

Gallbladder, Biliary and Pancreatic Disease

For gallbladder and biliary disease in the adult placebo-controlled studies, 3 patients with SBS were diagnosed with cholecystitis, all of whom had a prior history of gallbladder disease and were in the GATTEX 0.05 mg/kg/day dose group. No cases were reported in the placebo group. One of these 3 cases had gallbladder perforation and underwent cholecystectomy the next day. The remaining 2 cases underwent elective cholecystectomy at a later date. In the adult extension studies, 4 patients had an episode of acute cholecystitis; 3 patients had new-onset cholelithiasis; and 1 patient experienced cholestasis secondary to an obstructed biliary stent. For pancreatic disease in the adult placebo-controlled studies, 1 patient (GATTEX 0.05 mg/kg/day dose group) had a pancreatic pseudocyst diagnosed after 4 months of GATTEX. In the adult extension studies, 1 patient was diagnosed with chronic pancreatitis; and 1 patient was diagnosed with acute pancreatitis) [see Warnings and Precautions (5.3)].

Fluid Overload

In the adult placebo-controlled studies, peripheral edema was reported in 2/59 (3%) of patients on placebo and 8/77 (10%) patients on GATTEX; fluid overload was reported in 1/77 (1%) patient in the GATTEX group; no cases of fluid overload were seen in the placebo arm. There were 2 cases of congestive heart failure (CHF, 3%) in the GATTEX arm, 1 of which was reported as a serious adverse event and the other as non-serious. The serious case had onset at 6 months and was possibly associated with previously undiagnosed hypothyroidism and/or cardiac dysfunction [see Warnings and Precautions (5.4)].

Other Less Common Adverse Reactions

Reported in less than 5% of patients treated with GATTEX:

Gastrointestinal disorders: Colonic stenosis, Pancreatic duct stenosis, Small intestinal stenosis

Respiratory, thoracic and mediastinal disorders: Dyspnea

6.2 Postmarketing Experience

The following adverse reactions have been identified during post approval use of teduglutide. Because these reactions are reported voluntarily from a population of uncertain size, it is not always possible to reliably estimate their frequency or establish a causal relationship to drug exposure.

Gastrointestinal Neoplasia: colorectal polyps, gastric polyps, small intestinal polyps (duodenum, ileum, and jejunum)

Injection Site Reactions: injection site induration, inflammation, pruritus, urticaria, and warmth

7 DRUG INTERACTIONS

7.1 Potential for Increased Absorption of Oral Medications

Based upon the pharmacodynamic effect of GATTEX, there is a potential for increased absorption of concomitant oral medications. Altered mental status has been observed in patients taking GATTEX and benzodiazepines in the adult clinical studies [see Warnings and Precautions (5.5)].

Monitor patients on concomitant oral drugs requiring titration or with a narrow therapeutic index for adverse reactions related to the concomitant drug while on GATTEX. The concomitant drug may require a reduction in dosage.

8 USE IN SPECIFIC POPULATIONS

8.1 Pregnancy

Risk Summary

Available data from case reports with GATTEX use in pregnant women have not identified a drug-associated risk of major birth defects, miscarriage, or adverse maternal or fetal outcomes. Pregnant women with short bowel syndrome are at risk for malnutrition, which is associated with adverse maternal and fetal outcomes (see Clinical Considerations). In animal reproduction studies, no effects on embryo-fetal development were observed with the subcutaneous administration of teduglutide to pregnant rats and rabbits during organogenesis at exposures up to 686 and 657 times, respectively, the clinical exposure at the recommended human dose (based on AUC) (see Data).

The estimated background risk of major birth defects and miscarriage for the indicated population is unknown. All pregnancies have a background risk of birth defect, loss, or other adverse outcomes. In the U.S. general population, the estimated background risk of major birth defects and miscarriage in clinically recognized pregnancies is 2 to 4% and 15 to 20%, respectively.

Clinical Considerations

Disease-associated maternal and/or embryo/fetal risk

Pregnant women with short bowel syndrome are at risk for malnutrition. Severe malnutrition in pregnant women is associated with preterm delivery, low birth weight, intrauterine growth restriction, congenital malformations and perinatal mortality.

Data

Animal Data

Reproduction studies have been performed in pregnant rats at subcutaneous doses of teduglutide up to 25 mg/kg twice daily (50 mg/kg/day) (about 686 times the clinical exposure (AUC) at the recommended daily human dose of 0.05 mg/kg) and in pregnant rabbits at subcutaneous doses up to 25 mg/kg twice daily (50 mg/kg/day) (about 657 times the clinical exposure (AUC) at the recommended daily human dose of 0.05 mg/kg) during the period of organogenesis. These studies did not reveal any evidence of impaired fertility or harm to the fetus due to teduglutide. In a pre- and postnatal development study in rats (gestation day 7 to lactation day 20), teduglutide did not show any significant adverse effects on pre- and postnatal development at doses up to 25 mg/kg twice daily (50 mg/kg/day) (about 343 times the clinical exposure (AUC) at the recommended daily human dose of 0.05 mg/kg).

8.2 Lactation

Risk Summary

There is no information regarding the presence of GATTEX in human milk, the effects of GATTEX on the breastfed infant, or the effects of GATTEX on milk production. Teduglutide is present in the milk of lactating rats (see Data). Systemic exposure of teduglutide to a breastfed infant is expected to be low. However, because of the potential for serious adverse reactions in a breastfed infant, including tumorigenicity [see Nonclinical Toxicology (13.1)], advise patients that breastfeeding is not recommended during treatment with GATTEX.

Data

In a milk excretion study in the rat, a single subcutaneous dose of 25 mg/kg of teduglutide (81 times the recommended daily human dose of 0.05 mg/kg based on body surface area) was administered to lactating female rats at Day 12 postpartum. The maximum concentration of teduglutide in the milk corresponded to 0.9% and 2.9% of the plasma concentration at 1.5 and 4 hours after dosing, respectively.

8.4 Pediatric Use

The safety and effectiveness in pediatric patients less than 1 year of age have not been established.

The safety and effectiveness of GATTEX have been established in pediatric patients 1 year to less than 17 years of age who are dependent on parenteral support for the treatment of SBS. Use of GATTEX in this population is supported by evidence from adequate and well-controlled studies in adults, with additional efficacy, safety, pharmacokinetic and pharmacodynamic data in pediatric patients 1 year to less than 17 years of age [see Dosage and Administration (2), Adverse Reactions (6.1), Clinical Pharmacology (12.3), Clinical Studies (14.2)]. These data were derived from two studies of 24-week (Study 5) and 12-week (NCT01952080) duration in which 41 pediatric patients were treated with GATTEX in the following groups: 1 infant (1 year to less than 2 years), 37 children (2 years to less than 12 years) and 3 adolescents (12 years to less than 17 years).

In these 2 studies and the corresponding extension studies (Study 6 and NCT02949362), 29 pediatric patients were administered GATTEX prospectively for up to 94 weeks [see Clinical Studies (14.2)]. Adverse reactions in pediatric patients were similar to those seen in adults [see Adverse Reactions (6.1)].

Juvenile Animal Toxicity Data

In a juvenile toxicity study, teduglutide was administered to juvenile minipigs at subcutaneous doses of 0.5, 2.5 and 12.5 mg/kg twice daily (1, 5, and 25 mg/kg/day) from post-natal day 7 and continuing for 90 days). Exposures (AUC) at these doses were at least 12-, 25-, and 170-fold the pediatric clinical exposure for ages 1 year to 11 years at 0.05 mg/kg, respectively, and 10-, 21-, and 141-fold the pediatric clinical exposure for ages 12 years to 17 years at 0.05 mg/kg, respectively.

In juvenile minipigs, subcutaneous teduglutide caused intestinotrophic effects, gall bladder mucosal hyperplasia, bile duct mucosal hyperplasia, and injection site reactions, similar to those observed in adult animals.

8.5 Geriatric Use

Of the 134 patients with SBS that were treated with GATTEX at the recommended dosage of 0.05 mg/kg/day in the clinical studies, 19 patients were 65 years or older while 5 patients were 75 years of age or older. No overall differences in safety or efficacy were observed between these patients and younger patients, and other reported clinical experience has not identified differences in responses between the elderly and younger patients, but greater sensitivity of some older individuals cannot be ruled out [see Clinical Pharmacology (12.3)].

8.6 Renal Impairment

In adult subjects with moderate to severe renal impairment or end-stage renal disease (ESRD) (creatinine clearance <60 mL/min), the exposure to teduglutide increased with the degree of renal impairment [see Clinical Pharmacology (12.3)]. Reduce the dosage of GATTEX by half in both pediatric and adult patients with eGFR less than 60 mL/min/1.73 m^2 [see Dosage and Administration (2.3)].

8.7 Hepatic Impairment

GATTEX has not been studied in patients with severe hepatic impairment (Child-Pugh grade C). No dosage adjustment is recommended for patients with mild and moderate hepatic impairment (Child-Pugh grade A and B) [see Clinical Pharmacology (12.3)].

10 OVERDOSAGE

The maximum dose of GATTEX studied during clinical development was 80 mg/day for 8 days. No unexpected systemic adverse reactions were seen. In the event of overdose, the patient should be carefully monitored by the medical professional.

11 DESCRIPTION

The active ingredient in GATTEX (teduglutide) for injection is teduglutide, which is a 33 amino acid glucagon-like peptide-2 (GLP-2) analog manufactured using a strain of Escherichia coli modified by recombinant DNA technology. The chemical composition of teduglutide is L-histidyl-L-glycyl-L-aspartyl-L-glycyl-L-seryl-L-phenylalanyl-L-seryl-L-aspartyl-L-glutamyl-L-methionyl-L-asparaginyl-L-threonyl-L-isoleucyl-L-leucyl-L-aspartyl-L-asparaginyl-L-leucyl-L-alanyl-L-alanyl-L-arginyl-L-aspartyl-L-phenylalanyl-L-isoleucyl-L-asparaginyl-L-tryptophanyl-L-leucyl-L-isoleucyl-L-glutaminyl-L-threonyl-L-lysyl-L-isoleucyl-L-threonyl-L-aspartic acid. The structural formula is:

Figure 1: Structural formula of teduglutide

Teduglutide has a molecular weight of 3752 Daltons. Teduglutide drug substance is a clear, colorless to light-straw–colored liquid.

Each single-dose vial of GATTEX contains 5 mg of teduglutide as a white lyophilized powder for reconstitution and administration by subcutaneous injection. In addition to the active pharmaceutical ingredient (teduglutide), each vial of GATTEX contains 3.434 mg dibasic sodium phosphate heptahydrate, 3.88 mg L-histidine, 15 mg mannitol, and 0.644 mg monobasic sodium phosphate monohydrate as excipients. No preservatives are present.

At the time of administration, the lyophilized powder is reconstituted with 0.5 mL of Sterile Water for Injection, which is provided in a single-dose prefilled syringe. A 10 mg/mL sterile solution is obtained after reconstitution. Up to 0.38 mL of the reconstituted solution which contains 3.8 mg of teduglutide can be withdrawn for subcutaneous injection upon reconstitution.

12 CLINICAL PHARMACOLOGY

12.1 Mechanism of Action

Teduglutide is an analog of naturally occurring human glucagon-like peptide-2 (GLP-2), a peptide secreted by L-cells of the distal intestine. GLP-2 is known to increase intestinal and portal blood flow and inhibit gastric acid secretion. Teduglutide binds to the glucagon-like peptide-2 receptors located in intestinal subpopulations of enteroendocrine cells, subepithelial myofibroblasts and enteric neurons of the submucosal and myenteric plexus. Activation of these receptors results in the local release of multiple mediators including insulin-like growth factor (IGF)-1, nitric oxide and keratinocyte growth factor (KGF).

12.2 Pharmacodynamics

Intestinal Fluid Absorption

The ability of GATTEX to improve intestinal absorption was studied in 17 adult subjects with Short Bowel Syndrome (N=2-3 per dose group) using daily doses of 0.03, 0.1, 0.15 mg/kg (doses ranging from 0.6 to 3 times the recommended dose) in a 21-day, open-label, multicenter, dose-ranging study. All subcutaneous (abdomen) doses studied, except 0.03 mg/kg once daily, resulted in enhanced gastrointestinal fluid (wet weight) absorption of approximately 750 to 1000 mL/day, and increased villus height and crypt depth of the intestinal mucosa.

Cardiac Electrophysiology

At a dose 5 times the recommended dose, GATTEX did not prolong the QT interval to any clinically relevant extent.

12.3 Pharmacokinetics

Absorption

In healthy subjects, GATTEX administered subcutaneously had an absolute bioavailability of 88% and reached maximum plasma teduglutide concentrations at 3 to 5 hours after administration. Following a 0.05 mg/kg subcutaneous dose in SBS subjects, the median peak teduglutide concentration (Cmax) was 36 ng/mL and the median area under the curve at steady state (AUCtau) was 0.15 µg∙hr/mL. No accumulation of teduglutide was observed following repeated subcutaneous administrations.

The Cmax and AUC of teduglutide was dose proportional over the dose range of 0.05 to 0.4 mg/kg (up to 8 times the recommended dose of GATTEX).

Distribution

In healthy subjects, teduglutide has a volume of distribution (103 mL/kg) similar to blood volume.

Elimination

Metabolism

The metabolic pathway of teduglutide was not investigated in humans. However, teduglutide is expected to be degraded into small peptides and amino acids via catabolic pathways, similar to the catabolism of endogenous GLP-2.

Excretion

In healthy subjects, teduglutide plasma clearance was approximately 123 mL/hr/kg which is similar to the GFR suggesting that teduglutide is primarily cleared by the kidney. Teduglutide has a mean terminal half-life (t1/2) of approximately 2 hours in healthy subjects and 1.3 hours in SBS subjects.

Use in Specific Populations

Geriatric Patients

No differences were observed between healthy subjects younger than 65 years and those older than 65 years. Experience in subjects 75 years and above is limited.

Pediatric Patients

Following subcutaneous administration, similar steady state Cmax of teduglutide across age groups was demonstrated by population pharmacokinetics modeling (see Table 2). However, lower AUC was seen in pediatric patients 1 to 17 years of age as compared with adults and increases with increasing age.

Table 2: Teduglutide Pharmacokinetic Parameters Following Subcutaneous Dosing of GATTEX 0.05 mg/kg by Age Groups
Age | Parameters (Mean ± SD)
Age | Cmax, ss (ng/mL) | AUCss (ng∙h/mL) | CL/F (L/h) | t1/2 (h)
12 to 17 years (n=3) | 29.7 ± 8.4 | 154 ± 17.6 | 13.0 ± 2.3 | 1.0 ± 0.01
1 to 11 years (n=37) | 33.5 ± 11.5 | 128 ± 56.7 | 7.45 ± 2.1 | 0.7 ± 0.2

Male and Female Patients

No clinically relevant gender differences were observed.

Patients with Renal Impairment

In adult subjects with moderate to severe renal impairment or end stage renal disease (ESRD) (creatinine clearance <60 mL/min), the Cmax and AUC0-inf of teduglutide increased with the degree of renal impairment following a single subcutaneous dose of 10 mg GATTEX. Teduglutide exposure increased by a factor of 1.6, 1.4, and 2.1 (Cmax) and 1.5, 1.7, and 2.6 (AUC0-inf) in subjects with moderate, severe renal impairment and ESRD, respectively, compared to healthy subjects [see Dosage and Administration (2.3), Use in Specific Populations (8.6)].

Patients with Hepatic Impairment

Subjects with moderate hepatic impairment (Child-Pugh Class B) had an approximately 10 to 15% lower teduglutide Cmax and AUC compared to healthy matched control subjects after a single subcutaneous dose of 20 mg GATTEX. This reduction in teduglutide exposure is not thought to be clinically meaningful. GATTEX was not studied in subjects with severe hepatic impairment (Child-Pugh Class C).

Drug Interaction Studies

Clinical interaction studies were not performed. No inhibition or induction of the cytochrome P450 enzyme system has been observed based on in vitro studies although the relevance of in vitro studies to an in vivo setting is unknown.

12.6 Immunogenicity

The observed incidence of anti-drug antibodies is highly dependent on the sensitivity and specificity of the assay. Differences in assay methods preclude meaningful comparisons of the incidence of anti-drug antibodies in the studies described below with the incidence of anti-drug antibodies in other studies, including those of GATTEX or of other teduglutide products.

Adults

Based on integrated data from two studies in adults with SBS (a 6-month randomized placebo-controlled study, followed by a 24-month open-label study), the development of anti-teduglutide antibodies in patients who received subcutaneous administration of 0.05 mg/kg GATTEX once daily was 3% (2/60) at Month 3, 17% (13/77) at Month 6, 24% (16/67) at Month 12, 33% (11/33) at Month 24, and 48% (14/29) at Month 30. Anti-teduglutide antibodies were cross-reactive to native glucagon-like peptide (GLP-2) in 5 of the 6 patients (83%) who had anti-teduglutide antibodies and were tested for cross-reactivity. In the same two studies, a total of 36 patients were tested for neutralizing antibodies: one patient developed borderline positive neutralizing antibody responses at month 24 of the extension study. The antibody formation has not been associated with clinically relevant safety findings, reduced efficacy or changed pharmacokinetics of GATTEX.

Pediatric Patients 1 Year to Less than 17 Years of Age

In pediatric patients who received subcutaneous administration of 0.05 mg/kg GATTEX once daily for 24 weeks, the rate of anti-teduglutide antibody formation at Month 6 was 19% (5/26) and was similar to the rate of antibody formation in adult patients (17%). Of the 5 pediatric patients who had developed antibodies to teduglutide at Month 6, 2 patients had neutralizing antibodies. However, with the longer duration of treatment, the rate of anti-teduglutide formation at Month 12 was higher in pediatric patients with 54% (14/26), compared to that of adults (24%). Of the 14 pediatric patients who had developed antibodies to teduglutide at Month 12, 1 patient had neutralizing antibodies.

Among the small number of pediatric patients who developed anti-teduglutide antibodies, no association with adverse events or lack of efficacy was observed.

13 NONCLINICAL TOXICOLOGY

13.1 Carcinogenesis, Mutagenesis, Impairment of Fertility

Carcinogenic potential of GATTEX was assessed in 2-year subcutaneous carcinogenicity studies in rats and mice. In a 2-year carcinogenicity study in Wistar Han rats at subcutaneous doses of 3, 10, and 35 mg/kg/day (about 15, 41, and 199 times the exposures [AUC] achieved at the recommended daily human dose of 0.05 mg/kg, respectively), teduglutide caused statistically significant increases in the incidences of adenomas in the bile duct and jejunum of male rats. In a 2-year carcinogenicity study in Crl:CD1(ICR) mice at subcutaneous doses of 1, 3.5, and 12.5 mg/kg/day (about 32, 66, and 244 times the exposures [AUC] achieved at the recommended daily human dose of 0.05 mg/kg, respectively), teduglutide caused a significant increase in papillary adenomas in the gall bladder; it also caused adenocarcinomas in the jejunum in male mice at the high dose of 12.5 mg/kg/day.

Teduglutide was negative in the Ames test, chromosomal aberration test in Chinese hamster ovary cells, and in vivo mouse micronucleus assay.

Teduglutide at subcutaneous doses up to 25 mg/kg twice daily (50 mg/kg/day or at least 202 times the clinical exposure (AUC) at the recommended daily human dose of 0.05 mg/kg) was found to have no adverse effect on fertility and reproductive performance of male and female rats.

14 CLINICAL STUDIES

14.1 Treatment of SBS in Adults

Study 1 (Placebo-controlled) and Study 2 (Open-label Extension of Study 1)

Study 1 (CL0600-020, NCT00798967)

The efficacy, safety, and tolerability of GATTEX was evaluated in a randomized, double-blind, placebo-controlled, parallel-group, multi-national, multicenter clinical study (Study 1) in adults with SBS who were dependent on parenteral nutrition/intravenous (PN/I.V.) support for at least 12 months and required PN at least 3 times per week. For 8 weeks (or less) prior to randomization, investigators optimized the PN/I.V. volume of all patients. Optimization was followed by a 4-week to 8-week period of fluid stabilization. Patients then were randomized (1:1) to placebo (n=43) or GATTEX 0.05 mg/kg/day (n=43). Study treatment was administered subcutaneously once daily for 24 weeks. PN/I.V. volume adjustments (up to 30% decrease) and clinical assessments were made at 2, 4, 8, 12, 20, and 24 weeks.

The primary efficacy endpoint was based on a clinical response, defined as a patient achieving at least 20% reduction in weekly PN/I.V. volume from Baseline (immediately before randomization) to both Weeks 20 and 24.

The mean age of patients was 50 years. Mean duration of PN/I.V. dependency prior to enrollment was 6 years (range 1 to 26 years). The most common reasons for intestinal resection leading to SBS were vascular disease (34%, 29/85), Crohn's Disease (21%, 18/85), and "other" (21%, 18/85). Stoma was present in 45% (38/85) of patients, and the most common type was jejunostomy/ileostomy (82%, 31/38). The mean length of remaining small intestine was 77.3±64.4 cm (range: 5 to 343 cm). The colon was not in continuity in 44% (37/85) patients. At baseline, the mean (± SD) prescribed days per week for PN/I.V. infusion was 5.73 (±1.59) days.

The percentages of treatment group responders were compared in the intent-to-treat population of this study which was defined as all randomized patients. Sixty-three percent (27/43) of GATTEX-treated patients versus 30% (13/43) of placebo-treated patients were considered responders (p=0.002).

At Week 24, the mean reduction in weekly PN/I.V. volume was 4.4 Liters for GATTEX-treated patients (from pre-treatment baseline of 12.9 Liters) versus 2.3 Liters for placebo-treated patients (from pre-treatment baseline of 13.2 Liters/week) (p<0.001).

Twenty-one patients on GATTEX (54%) versus 9 on placebo (23%) achieved at least a one-day reduction in PN/I.V. support.

The mean changes from Baseline in PN/I.V. volume by visit are shown in Figure 2.

Figure 2: Change (±95% CI) in PN/I.V. volume (L/week)

Study 2 (CL0600-021, NCT00930644)

Study 2 was a 2-year open-label extension of Study 1 in which 88 patients received GATTEX 0.05 mg/kg/day. Ninety-seven percent (76/78) of patients who completed Study 1 elected to enroll in Study 2 (37 received GATTEX; 39 received Placebo). An additional 12 patients entered Study 2, who had been optimized and stabilized but not randomized in Study 1 because of closed enrollment.

30 months exposure

Thirty GATTEX patients completed a total duration of 30 months (Study 1 followed by Study 2 treatment). Of these, 28 patients (93%) achieved a 20% or greater reduction of parenteral support (PS). Of responders in Study 1 who had completed 2 additional years of continuous treatment with GATTEX, 96% (21/22) sustained their response to GATTEX. The mean reduction in PN/I.V. (n=30) was 7.55 L/week (a 66% reduction from baseline). Ten patients were weaned off their PN/I.V. support while on GATTEX treatment for 30 months. Patients were maintained on GATTEX even if no longer requiring PN/I.V. support. These 10 patients had required PN/I.V. support for 1.2 to 15.5 years, and prior to GATTEX had required between 3.5 L/week and 13.4 L/week of PN/I.V. support. At the end of study, 21 (70%), 18 (60%) and 18 (60%) of the 30 completers achieved a reduction of 1, 2, or 3 days per week in PN/I.V. support, respectively.

24 months exposure

Of the 39 placebo-treated patients from Study 1 entering Study 2, 29 completed 24 months of treatment with GATTEX. The mean reduction in PN/I.V. was 3.11 L/week (an additional 28.3% reduction) from the start of Study 2. Sixteen (55%) of the 29 completers achieved a 20% or greater reduction of PS. At the end of the study, 14 (48%), 7 (24%) and 5 (17%) achieved a reduction of 1, 2, or 3 days per week in PN/I.V. support, respectively. Two patients were weaned off their PN/I.V. support while on GATTEX. Of the 12 patients entering Study 2 directly, 6 completed 24 months of treatment with GATTEX. Similar effects were seen. One of the six patients was weaned off their PN/I.V. support while on GATTEX.

Study 3 (Placebo-controlled) and Study 4 (Blinded Uncontrolled Extension of Study 3)

Study 3 (CL0600-004, NCT00081458)

Study 3 was a randomized, double-blind, placebo-controlled, three parallel-group, multinational study in adults with SBS who were dependent on parenteral nutrition/intravenous (PN/I.V.) support for at least 12 months and required PN at least 3 times per week. After a period of optimization and stabilization similar to Study 1, patients were randomized to receive 24 weeks of one of the following treatment regimens: GATTEX 0.05 mg/kg/day (n=35), GATTEX 0.1 mg/kg/day (twice the recommended dose) (n=33), or placebo (n=16). GATTEX 0.1 mg/kg/day is not a recommended dosage [see Dosage and Administration (2.2)]. The treatment groups were compared using the intent-to-treat population of this study which was defined as all randomized patients who were administered at least one dose of study drug. This population contained one less patient in the 0.1 mg/kg/day dose group hence n=32 in this group for all analyses. The primary efficacy endpoint was a graded categorical score that did not achieve statistical significance for the high dose. Further evaluation of PN/I.V. volume reduction using the endpoint of response (defined as at least 20% reduction in PN/I.V. fluid from Baseline to Weeks 20 and 24) showed that 46% of patients on GATTEX 0.05 mg/kg/day responded versus 6% on placebo. Patients on GATTEX in both dose groups experienced a 2.5 L/week reduction in PS requirements versus 0.9 L/week for placebo at 24 weeks. Two patients in the GATTEX 0.05 mg/kg/day dose group were weaned off PS by Week 24.

Study 4 (CL0600-005, NCT00172185)

Study 4 was a blinded, uncontrolled extension of Study 3, in which 65 patients from Study 3 received GATTEX for up to an additional 28 weeks of treatment. Of responders in Study 3 who entered Study 4, 75% sustained response on GATTEX after one year of treatment. In the GATTEX 0.05 mg/kg/day dose group, a 20% or greater reduction of PS was achieved in 68% (17/25) of patients. The mean reduction of weekly PN/I.V. volume was 4.9 L/week (52% reduction from baseline) after one year of continuous GATTEX treatment. The patients who had been completely weaned off PN/I.V. support in Study 3 remained off PS through Study 4. During Study 4, an additional patient from Study 3 was weaned off PS.

14.2 Treatment of SBS in Pediatric Patients

Study 5 (TED-C14-006, NCT02682381)

Study 5 was a 24-week, multicenter study conducted in 59 pediatric patients aged 1 year through 17 years with SBS who were dependent on PS. Patients chose whether to receive GATTEX or standard of care (SOC). Patients who chose to receive GATTEX treatment were subsequently randomized in a double-blind manner to 0.025 mg/kg/day (n=24) or 0.05 mg/kg/day (n=26), while 9 patients enrolled in the SOC arm. Randomization to the GATTEX dose groups was stratified by age.

Patients treated with 0.05 mg/kg had a mean age of 6 years at baseline. The most common reasons for intestinal resection leading to SBS were gastroschisis (54%, 14/26), midgut volvulus (23%, 6/26), and necrotizing enterocolitis (12%, 3/26). Stoma was present in 19% (5/26) of patients, and the most common type was jejunostomy (80%, 4/5). The mean length of remaining small intestine was 47 (±28) cm (range: 9 to 120 cm). In the 25 patients who had remaining colon, the colon was in continuity in 22 patients. At baseline, the mean PS volume was 60 (±29) mL/kg/day (range: 24 to 133 mL/kg/day) [8 (±4) L/week (range: 3 to 19 L/week)] and mean PS infusion time was 7 (±1) days/week (range: 5 to 7 days/week) and 11 (±3) hours/day (range: 7 to 20 hours/day).

Results described in Table 3 correspond to the recommended GATTEX dosage of 0.05 mg/kg subcutaneously once daily.

Table 3: Summary of Efficacy Endpoints at Week 24 [Results based on patient diary data, ITT population] for Study 5 – Patients treated with GATTEX 0.05 mg/kg/day (N = 26)
Efficacy Endpoints | Results
Reduction in PS volume of at least 20%, n/N (%) | 18/26 (69%)
Achieved enteral autonomy, n/N (%) | 3/26 (12%)
Reduction in PS infusion of ≥1 day/week, n/N (%) | 10/26 (38%)
Change in PS volume from baseline (mL/kg/day), mean (SD) and [mean% (SD)] | -23 (18) mL/kg/day [-42% (29%)]

Study 6 (SHP633-304, NCT02954458)

Study 6 was a prospective, open-label, long-term extension study of pediatric patients who completed Study 5. In the extension study, patients received additional treatment with GATTEX 0.05 mg/kg subcutaneously once daily if they deteriorated or stopped improving after discontinuation of prior GATTEX treatment. Of the 15 patients who initially responded in Study 5 and enrolled in Study 6, 13 patients (87%) required additional treatment with GATTEX. Efficacy results at the end of the first 24-week treatment period in Study 6 (total treatment for a mean of 40 weeks) were similar to those achieved at the end of 24 weeks treatment in Study 5. One additional patient treated with 0.05 mg/kg in Study 5 eventually achieved enteral autonomy during follow-up in Study 6.

16 HOW SUPPLIED/STORAGE AND HANDLING

GATTEX (teduglutide) for injection is supplied as 5 mg of teduglutide as a white, lyophilized powder for reconstitution in a sterile, single-dose glass vial with 0.5 mL Sterile Water for Injection in a single-dose prefilled syringe. The product to be dispensed is either a one-vial kit or a 30-vial kit.

One-vial kits are pre-assembled and ready to be used:

GATTEX 5 mg One-vial Kit (NDC 68875-0103-1):

- One single-dose vial of 5 mg teduglutide (NDC 68875-0101-1)
- One disposable prefilled syringe containing 0.5 mL Sterile Water for Injection USP for reconstitution, with a separate needle (23G × 1½ in) to attach to the syringe
- One sterile disposable 1 mL syringe with needle (27G × 1/2 in) for dosing
- Four alcohol swabs

Storage and Handling of One-Vial Kit

Prior to Dispensing:

- Store GATTEX 5 mg Strength one-vial kits refrigerated at 2°C to 8°C (36°F to 46°F). Do not freeze. Do not use beyond the expiration date on the label.

After Dispensing by the Pharmacist:

- Store GATTEX 5 mg Strength one-vial kits at room temperature up to 25°C (77°F). Do not freeze. Dispense with a 90-day "use by" dating.

GATTEX is also supplied in 30-vial cartons to be assembled by the dispensing pharmacist into a 30-vial kit by transferring the trays containing 30 vials from a Carton of Drug Vials into a Carton of Ancillary Supplies:

GATTEX 5 mg Carton of Drug Vials (NDC 68875-0101-2):

- Thirty single-dose vials of GATTEX 5 mg (NDC 68875-0101-1)
- Carton of Ancillary Supplies:
  - Thirty disposable prefilled syringes containing diluent (0.5 mL Sterile Water for Injection USP) for reconstitution
  - Thirty separate needles (23G × 1½ in) to attach to the syringes for reconstitution
  - Thirty sterile disposable 1 mL syringes with needle (27G × 1/2 in)
  - Sixty alcohol swabs

The final assembled 30-Vial Kit should contain the items:

GATTEX 5 mg Strength 30-Vial Kit (NDC 68875-0102-1):

- Thirty single-dose vials of 5 mg teduglutide (NDC 68875-0101-1)
- Thirty disposable prefilled syringes containing 0.5 mL Sterile Water for Injection USP for reconstitution, with 30 separate needles (23G × 1½ in) to attach to the syringes
- Thirty sterile disposable 1 mL syringes with needle (27G × 1/2 in) for dosing
- Sixty alcohol swabs

Storage and Handling of 30-Vial Cartons and 30-Vial Kits

Prior to Dispensing:

- Store GATTEX 5 mg vials refrigerated at 2°C to 8°C (36°F to 46°F). Do not freeze. Do not use beyond the expiration date on the label.
- Store the Carton of Ancillary Supplies at room temperature up to 25°C (77°F).

After Dispensing by the Pharmacist:

- Store GATTEX 5 mg Strength 30-vial kits at room temperature up to 25°C (77°F). Do not freeze. Dispense with a 90-day "use by" dating.

17 PATIENT COUNSELING INFORMATION

Advise the patient to read the FDA-approved patient labeling (Medication Guide and Instructions for Use).

Acceleration of Neoplastic Growth

Advise adult patients and their caregivers that the patient will need to undergo clinical examinations, repeated colonoscopies and upper GI endoscopies (or alternate imaging) before and during treatment with GATTEX to monitor for the development of polyps and/or neoplasia of the GI tract. Advise pediatric patients and their caregivers that the patient will need to undergo clinical examinations, fecal occult blood testing before and during treatment and colonoscopies after 1 year of treatment, every 5 years thereafter while on continuous treatment with GATTEX or if they have new or unexplained gastrointestinal bleeding. Advise pediatric patients and their caregivers that an upper GI endoscopy will be performed if there is any new or unexplained blood in the stool [see Warnings and Precautions (5.1)].

Intestinal Obstruction

Advise patients and their caregivers to immediately contact their healthcare provider if they experience any symptoms suggestive of intestinal or stomal obstruction [see Warnings and Precautions (5.2)].

Biliary and Pancreatic Disease

Advise patients and their caregivers that laboratory assessments will be done periodically while on GATTEX to monitor for the onset or worsening of gallbladder, biliary and pancreatic disease, and to report immediately to their healthcare provider if they develop symptoms suggestive of cholecystitis, cholangitis, cholelithiasis or pancreatic disease [see Warnings and Precautions (5.3)].

Fluid Overload

Advise patients and their caregivers to immediately contact their healthcare provider if they develop fluid overload or symptoms of congestive heart failure while on GATTEX [see Warnings and Precautions (5.4)].

Fluid Imbalance

Advise patients and their caregivers of the risk of fluid and electrolyte imbalance with discontinuation of GATTEX, and to contact their healthcare provider if they develop symptoms suggestive of electrolyte imbalances [see Warnings and Precautions (5.4)].

Increased Absorption of Concomitant Oral Medication

Instruct patients and their caregivers to report to their healthcare provider any concomitant oral medications that they are taking in order to assess any potential for increased absorption during GATTEX treatment of those oral medications requiring titration or with a narrow therapeutic index [see Warnings and Precautions (5.5)].

Lactation

Advise women that breastfeeding is not recommended during treatment with GATTEX [see Use in Specific Populations (8.2)].

GATTEX and are registered trademarks of Takeda Pharmaceuticals U.S.A., Inc.
©2025 Takeda Pharmaceutical Company Limited. All rights reserved.
Patented: see www.takeda.com/en-us/patents.

Distributed by:
Takeda Pharmaceuticals America, Inc.
Cambridge, MA 02142
USA

For information about GATTEX contact:
Takeda Pharmaceuticals America, Inc.
Cambridge, MA 02142
USA
1-877-825-3327
www.GATTEX.com

MEDICATION GUIDE
GATTEX® (Ga'-tex)
(teduglutide)
for injection, for subcutaneous use

Read this Medication Guide carefully before you start taking GATTEX and each time you get a refill. There may be new information. This information does not take the place of talking with your healthcare provider about your medical condition or your treatment.

What is the most important information I should know about GATTEX?
GATTEX may cause serious side effects, including:

- Making abnormal cells grow faster.
  - GATTEX can make abnormal cells that are already in your body grow faster. There is an increased risk that abnormal cells could become cancer. If you get cancer of the bowel (intestines), liver, gallbladder, or pancreas while using GATTEX, your healthcare provider should stop GATTEX.
  - If you get other types of cancers, you and your healthcare provider should discuss the risks and benefits of using GATTEX.
- Polyps in the intestines. Polyps are growths on the inside of the intestines.

Before you start using GATTEX, your healthcare provider will:

For Adult Patients

- Have your colon and upper intestines checked for polyps within 6 months before starting GATTEX.
- Have any polyps removed.

For Pediatric Patients

- Check for blood in the stool within 6 months before starting GATTEX.
- If there is blood found in the stool, have your colon and upper intestines checked for polyps.
- Have any polyps removed.

To keep using GATTEX, your healthcare provider should:

For Adult Patients

- Have your colon and upper intestines checked for new polyps at the end of 1 year of using GATTEX. If no polyp is found, your healthcare provider should check you for polyps as needed and at least every 5 years.
- Have any new polyps removed.

For Pediatric Patients

- Check for blood in the stool every year while using GATTEX.
- If there is blood found in the stool, have your colon and upper intestines checked for polyps.
- Have your colon checked for new polyps at the end of 1 year of using GATTEX. If no polyp is found, your healthcare provider should check you for polyps as needed and at least every 5 years.
- Have any new polyps removed.

If cancer is found in a polyp, your healthcare provider should stop GATTEX.

- Blockage of the bowel (intestines).
  A bowel blockage keeps food, fluids, and gas from moving through the bowels in the normal way. Tell your healthcare provider right away if you have any of these symptoms of a bowel or stomal blockage:

- trouble having a bowel movement or passing gas
- stomach area (abdomen) pain or swelling
- nausea

- vomiting
- swelling and blockage of your stoma opening, if you have a stoma

If a blockage is found, your healthcare provider may temporarily stop GATTEX.

- Swelling (inflammation) or blockage of your gallbladder or pancreas.
  Your healthcare provider will do tests to check your gallbladder and pancreas within 6 months before starting GATTEX and at least every 6 months while you are using GATTEX.

Tell your healthcare provider right away if you get:

- stomach area (abdomen) pain and tenderness
- chills
- fever
- a change in your stools

- nausea
- vomiting
- dark urine
- yellowing of your skin or the whites of eyes

These are not all the side effects of GATTEX. For more information, see "What are the possible side effects of GATTEX?"

What is GATTEX?

- GATTEX is a prescription medicine used in adults and children 1 year of age and older with Short Bowel Syndrome (SBS) who need additional nutrition or fluids from intravenous (IV) feeding (parenteral support).
- It is not known if GATTEX is safe and effective in children under 1 year of age.

What should I tell my healthcare provider before using GATTEX?
Before using GATTEX, tell your healthcare provider about all your medical conditions, including if you or your child:

- have cancer or a history of cancer.
- have or had polyps anywhere in your bowel (intestines) or rectum.
- have heart problems.
- have high blood pressure.
- have problems with your gallbladder, pancreas, or kidneys.
- are pregnant or plan to become pregnant. It is not known if GATTEX will harm your unborn baby. Tell your healthcare provider right away if you become pregnant while using GATTEX.
- are breastfeeding or plan to breastfeed. It is not known if GATTEX passes into your breast milk. Talk to your healthcare provider about the best way to feed your baby while using GATTEX. Breastfeeding is not recommended during treatment with GATTEX.

Tell your healthcare providers about all the medicines you take, including prescription and over-the-counter medicines, vitamins, and herbal supplements. Using GATTEX with certain other medicines may affect each other causing side effects. Your other healthcare providers may need to change the dose of any oral medicines (medicines taken by mouth) you take while using GATTEX. Tell the healthcare provider who gives you GATTEX if you will be taking a new oral medicine.
Know the medicines you take. Keep a list of them to show your healthcare provider and pharmacist when you get a new medicine.

How should I use GATTEX?

- Use GATTEX exactly as your healthcare provider tells you to.
- Your healthcare provider or nurse should show you how to prepare, measure your dose, and give your injection of GATTEX. Self-administration is not recommended in pediatric patients.
- GATTEX comes as a 5 mg kit. Use of the GATTEX 5 mg kit is not recommended in pediatric patients weighing less than 22 pounds (10 kg).
- GATTEX is given 1 time each day at the same time.
- Inject your dose of GATTEX under the skin (subcutaneous injection) in your stomach area (abdomen), upper legs (thighs), or upper arms. Do not inject GATTEX into a vein or muscle.
- Use a different injection site each time you use GATTEX.
- GATTEX comes as a powder for injection in a vial that is used only 1 time (single dose vial). The powder must be mixed with Sterile Water for Injection (a diluent) provided in a prefilled syringe before you inject it.
- GATTEX must be injected within 3 hours after you mix it with the diluent.
- If you miss a dose, take it as soon as you remember that day. Take your next dose the next day at the same time you take it every day.
- Do not take 2 doses on the same day.
- If you use more than 1 dose, call your healthcare provider right away.
- Do not stop taking GATTEX without consulting your healthcare provider.
- Read the Instructions for Use for detailed instructions for preparing and injecting a dose of GATTEX.

What are the possible side effects of GATTEX?
GATTEX may cause serious side effects, including:

- See "What is the most important information I should know about GATTEX?"
- Fluid overload. Your healthcare provider will check you for too much fluid in your body. Too much fluid in your body may lead to heart failure, especially if you have heart problems. Tell your healthcare provider right away if you get swelling in your feet and ankles, you gain weight very quickly (water weight), or you have trouble breathing.

The most common side effects of GATTEX in adults include:

- stomach area (abdomen) pain or swelling
- nausea
- cold or flu symptoms
- skin reaction where the injection was given (such as redness, pain, swelling, itching, or hives)

- vomiting
- swelling of the hands or feet
- allergic reactions

The side effects of GATTEX in pediatric patients are similar to those seen in adults.
Tell your healthcare provider if you have any side effect that bothers you or that does not go away.
These are not all of the possible side effects of GATTEX.
Call your doctor for medical advice about side effects. You may report side effects to FDA at 1-800-FDA-1088.

How should I store GATTEX?

- Store GATTEX powder at room temperature up to 77°F (25°C).
- Do not freeze GATTEX.
- Use the GATTEX powder by the expiration date on the "Use By" sticker on the kit.
- Use GATTEX within 3 hours after mixing it.
- Throw away any unused GATTEX that has been mixed, even if there is medicine left in the vial.
- Do not store any GATTEX you have mixed.

Keep GATTEX and all medicines out of the reach of children.

General information about the safe and effective use of GATTEX.
Medicines are sometimes prescribed for purposes other than those listed in a Medication Guide. Do not use GATTEX for a condition for which it was not prescribed. Do not give GATTEX to other people, even if they have the same symptoms that you have. It may harm them.
If you would like more information about GATTEX talk with your healthcare provider. You can ask your healthcare provider or pharmacist for information about GATTEX that is written for health professionals.

What are the ingredients in GATTEX?
Active ingredient: teduglutide

Inactive ingredients: dibasic sodium phosphate heptahydrate, L-histidine, mannitol, and monobasic sodium phosphate monohydrate. Sterile Water for Injection is provided as a diluent.
Distributed by:
Takeda Pharmaceuticals America, Inc.
Cambridge, MA 02142
GATTEX and are registered trademarks of Takeda Pharmaceuticals U.S.A., Inc.
©2025 Takeda Pharmaceutical Company Limited. All rights reserved.
Patented: see www.takeda.com/en-us/patents.

This Medication Guide has been approved by the U.S. Food and Drug Administration

Revised: 09/2025

Instructions for Use GATTEX®(Ga'-tex) (teduglutide) for injection, for subcutaneous use 5 mg per vial

This Instructions for Use contains information on how to inject GATTEX.

Read this Instructions for Use before you start using GATTEX and each time you get a refill. There may be new information. Your healthcare provider or nurse should show you how to prepare, measure your dose, and give your injection of GATTEX the right way.

If you cannot give yourself the injection:

- ask your healthcare provider or nurse to help you, or
- ask someone who has been trained by a healthcare provider or nurse to give your injections.

Self-administration is not recommended in pediatric patients. In pediatric patients, GATTEX should be injected by:

- a healthcare provider or nurse, or
- a parent or adult caregiver who has been trained by a healthcare provider or nurse to give injections of GATTEX to pediatric patients.

Important information:

- Use of the GATTEX 5 mg kit is not recommended in pediatric patients weighing less than 22 pounds (10 kg).
- Before you start, check the "Use By" date on your GATTEX kit. Make sure that the "Use By" date has not passed. Do not use anything in the GATTEX kit after the "Use By" date on the kit.
- Give GATTEX within 3 hours after you mix the powder with the Diluent (Sterile Water for Injection).
- Use the syringes and needles provided in the GATTEX kit.
- Do not use a GATTEX vial more than 1 time, even if there is medicine left in the vial.
- Throw away (dispose of) any unused GATTEX after you give your injection.
- Safely throw away GATTEX vials after use.
- Do not re-use syringes or needles. See "Step 7: Dispose of syringes and needles" for information about how to safely throw away needles and syringes.
- To help avoid needle-stick injuries, do not recap needles.

Gather the supplies you will need to prepare GATTEX and to give your injection (See Figure A).

Figure A

From your GATTEX kit you will need:

- 5 mg vial of GATTEX with green cap.
  Your healthcare provider will tell you how many vials of GATTEX you will need for your injection.
- 2 alcohol swab pads
- Diluent syringe with a white snap-off cap
- Needle for reconstitution (23G, 1½ inch)
- Plastic dosing syringe (1 mL) with needle attached (27G, 1/2 inch)
- A sharps disposal container (not included in the GATTEX kit). See "Step 7: Dispose of needles and syringes."

You may also need an adhesive bandage (not included in your GATTEX kit).

Step 1: Prepare the injection.

- Choose a well-lit, clean, flat work surface.
- Wash your hands with soap and water.

Step 2: Preparing the Diluent syringe.

- Put the Diluent syringe (See Figure B1) and the 23G, 1½ inch needle in front of you on your work surface.

Figure B1

- Hold the Diluent syringe by the barrel. Snap off the white cap (bend the cap sideways until the cap comes off). Only the top portion of the white cap should be snapped off. The lower portion of the cap will remain in place (See Figure B2). Throw the cap away.

Figure B2

- Remove the 23G, 1½ inch needle from the package. Use the fold in the package to peel back the plastic cover (See Figure C). Leave the plastic cap on the needle.

Figure C

- Push the open end of the needle onto the end of the Diluent syringe (See Figure D).
  Twist the needle clockwise (to the right) until it stops turning.

Figure D

- When the needle is tightly in place, put the Diluent syringe and needle on your work surface.

Step 3: Mix GATTEX powder with Diluent.

- Remove the green cap from the GATTEX vial. Throw away the green cap.
- Find the gray rubber seal on top of the GATTEX vial (See Figure E).

Figure E

- Use an alcohol swab pad to clean the gray rubber seal (See Figure F).
- Do not touch the gray rubber seal after you clean it.

Figure F

- Pick up the Diluent syringe with the needle attached.
- Remove the plastic cap that covers the needle (See Figure G). Throw the cap away.

Figure G

- Hold the GATTEX vial between your thumb and index (pointer) finger (See Figure H). Be careful not to touch the gray rubber seal.
- Push the needle down through the center of the gray rubber seal.
- Slowly push down on the plunger of the Diluent syringe. Empty all the Diluent into the GATTEX vial.
- Leave the needle and Diluent syringe in place.

Figure H

- Gently tap the barrel of the Diluent syringe with a finger (See Figure I).
- Make sure all the Diluent has gone into the GATTEX vial.

Figure I

- Remove the Diluent syringe and needle from the GATTEX vial. Let the vial sit for about 30 seconds.
- Do not put the needle cap back on the needle.
- Throw away (dispose of) the Diluent syringe and needle in your sharps disposal container.
- After 30 seconds, place the GATTEX vial between the palms of your hands. Gently roll the vial for about 15 seconds (See Figure J).
- Do not shake the GATTEX vial.
- Do not touch the gray rubber seal. If you do, clean it again with a new alcohol pad.
- Let the GATTEX vial stand on your work surface for about 2 minutes.

Figure J

Step 4: Check the mixed GATTEX.

- After 2 minutes, look at the vial of GATTEX. The liquid in the vial should be clear and colorless to pale yellow, and should not have any particles in it.
- If there is any powder in the GATTEX vial that did not dissolve, gently roll the vial between your hands for 15 seconds more.
- Do not shake the GATTEX vial.
- Check the GATTEX vial again for anything that did not dissolve.
- Do not use the GATTEX vial if there is anything in it that did not dissolve. Start from the beginning of this Instructions for Use to prepare a new vial. Use a new GATTEX vial, new Diluent syringe, and a new needle.

Step 5: Draw up your dose of GATTEX.

- Remove the plastic dosing syringe from the package. Use the fold in the package to peel back the plastic cover (See Figure K).

Figure K

- Remove the needle cap from the plastic dosing syringe (See Figure L).
- Throw the needle cap away. Do not touch the needle or allow it to touch anything.

Figure L

- Carefully pull back on the plunger to the line that matches the dose prescribed by your healthcare provider.
- Use 1 hand to hold the GATTEX vial steady. Use your other hand to insert the needle straight down into the middle of the gray rubber seal on the GATTEX vial (See Figure M). You may feel some resistance as the needle passes through the rubber seal.
- Gently push down the plunger until all of the air has gone from the plastic dosing syringe into the GATTEX vial.
- Turn the GATTEX vial and plastic dosing syringe upside down (See Figure N).

Figure M

Figure N

- Hold the GATTEX vial with 1 hand.
- Slowly pull back the plunger of the plastic dosing syringe with your other hand.
- Fill the plastic dosing syringe until the black tip of the plunger lines up with the mark that matches your prescribed dose (See Figure O).
- Keep the plastic dosing syringe and needle in the GATTEX vial.

Figure O

- You may see some bubbles inside the GATTEX vial when the plastic dosing syringe is filled. This is normal. With the needle still in the vial, gently tap the side of the plastic dosing syringe with a finger to make any air bubbles rise to the top (See Figure P).

Figure P

- Slowly push the plunger up until all air bubbles are out of the plastic dosing syringe. Make sure the tip of the needle is in the fluid. Slowly pull back the plunger to draw up the right dose of GATTEX into the plastic dosing syringe.
- Remove the plastic dosing syringe and needle from the GATTEX vial (See Figure Q). Do not touch the needle or allow it to touch anything.

Figure Q

Step 6: Inject GATTEX.

- Choose an injection site on the stomach area (abdomen), thighs, or upper arms.
- Choose a different site to give the injection each day. Do not inject into areas where the skin is tender, bruised, red, or hard. (See Figure R and Figure S)

Figure R

Figure S

- Clean the skin where you plan to give the injection with a new alcohol swab pad. Do not touch this area again before giving the injection.
- Use 1 hand to gently pinch up a fold of skin around the injection site (See Figure T).

Figure T

- Use your other hand to hold the plastic dosing syringe. Insert the full length of the needle into the skin at a 45-degree angle with a quick, "dart-like" motion (See Figure U).

Figure U

- Let go of the skin. Hold the syringe barrel with 1 hand while you slowly push down the plunger until the plastic dosing syringe is empty (See Figure V).

Figure V

- When the plastic dosing syringe is empty, quickly pull the needle out of your skin. There may be a little bleeding at the injection site. Apply an adhesive bandage to the injection site if needed.

Step 7: Dispose of syringes and needles.

- Do not re-use a syringe or needle.
- To help avoid needle-stick injuries, do not recap a needle.
- Put your needles and syringes in an FDA-cleared sharps disposal container right away after use. Do not throw away (dispose of) loose needles and syringes in your household trash.
- If you do not have an FDA-cleared sharps disposal container, you may use a household container that is:
  - made of heavy-duty plastic,
  - can be closed with a tight-fitting, puncture-resistant lid, without sharp items being able to come out,
  - upright and stable during use,
  - leak-resistant, and
  - properly labeled to warn of hazardous waste inside the container.
- When your sharps disposal container is almost full, you will need to follow your community guidelines for the right way to dispose of your sharps disposal container.
  There may be local or state laws about how to throw away syringes and needles. For more information about safe sharps disposal, and for specific information about sharps disposal in the state that you live in, go to the FDA's website at: http://www.fda.gov/safesharpsdisposal.
- Do not dispose of your sharps disposal container in your household trash unless your community guidelines permit this. Do not recycle your sharps disposal container.
- Throw away the GATTEX vial into the container where you put the syringes and needles.
- If you have any questions, talk to your healthcare provider or pharmacist.

How should I store GATTEX?

- Store GATTEX powder at room temperature up to 77°F (25°C).
- Do not freeze GATTEX.
- Use the GATTEX powder by the expiration date on the "Use By" sticker on the kit.
- Use GATTEX within 3 hours after mixing it.
- Throw away any unused GATTEX that has been mixed, even if there is medicine left in the vial.
- Do not store any GATTEX you have mixed.

Keep GATTEX and all medicines out of the reach of children.

Distributed by:
Takeda Pharmaceuticals America, Inc.
Cambridge, MA 02142
USA
1-877-825-3327

GATTEX and are registered trademarks of Takeda Pharmaceuticals U.S.A., Inc.

©2025 Takeda Pharmaceutical Company Limited. All rights reserved.

This Instructions for Use has been approved by the U.S. Food and Drug Administration.

Revised: 09/2025

PRINCIPAL DISPLAY PANEL - 5 mg Vial Carton

NDC 68875-0101-2

Gattex®
(teduglutide) for injection

5 mg

5 mg per vial.
For subcutaneous use only.

EACH CARTON CONTAINS:

- Thirty single-dose vials of Gattex®
- Package Insert
- Medication Guide

ATTENTION PHARMACIST:

- For dispensing, transfer the product with vial trays
  from this carton into the 30-count patient kit.

Takeda

PRINCIPAL DISPLAY PANEL - Kit Carton - 68875-0103

NDC 68875-0103-1

Rx only

Gattex®
(teduglutide) for injection

5 mg

Pharmacy:
Apply Use By dating
sticker here

5 mg per vial.
For subcutaneous use only.

Attention Patients: Store at room temperature up to 25°C (77°F). Do not freeze.

Takeda

PRINCIPAL DISPLAY PANEL - Kit Carton - 68875-0102

Rx only

Pharmacy:
Apply Use By dating
sticker here

NDC 68875-0102-1

Gattex®
(teduglutide) for injection

5 mg

5 mg per vial.
For subcutaneous use only.

Takeda